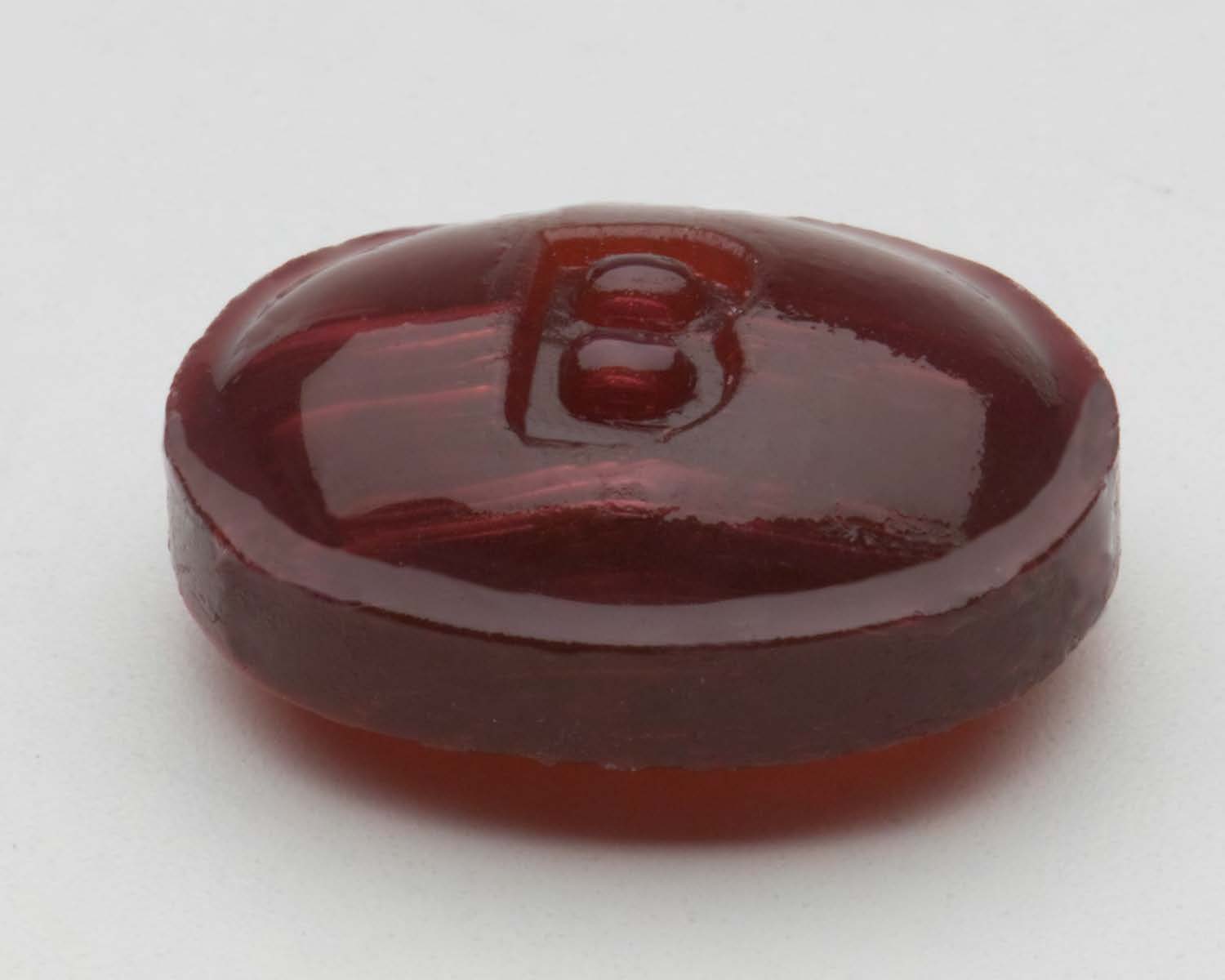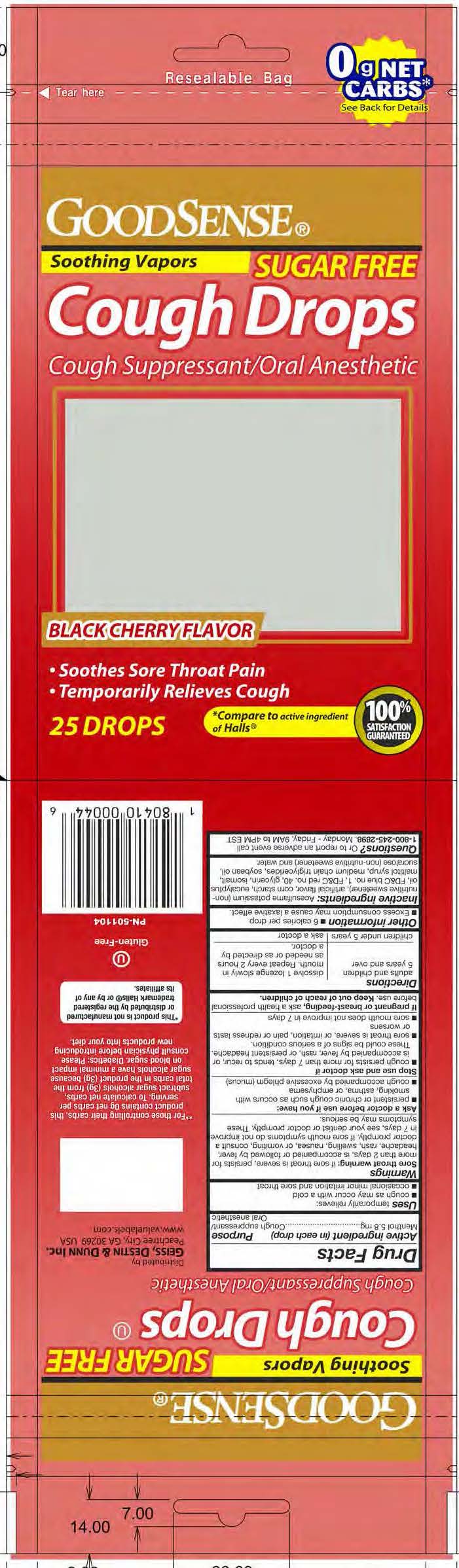 DRUG LABEL: sugar free cherry cough drops
NDC: 75981-006 | Form: LOZENGE
Manufacturer: Geiss, Destin & Dunn
Category: otc | Type: HUMAN OTC DRUG LABEL
Date: 20211027

ACTIVE INGREDIENTS: MENTHOL 5.8 mg/1 1
INACTIVE INGREDIENTS: WATER

Menthol 5.8 mg

Active ingredient (in each drop)

Menthol 5.8 mg

Purpose

Cough suppressant / Oral anesthetic

INDICATIONS AND USAGE

Uses temporarily relieves:

cough as may occur with a cold

occasional minor irritation and sore throat

Warnings

Sore throat warning: if sore throat is severe, persists for more than 2 days, is accompanied or followed be fever, headache, rash, swelling, nausea, or vomiting, consult a doctor promptly. If sore mouth symptoms do not improve in 7 days, see your dentist or doctor promptly. These symptoms may be serious.

Ask a doctor before use if you have:

- persistent or chronic cough such as occus with smoking, asthma, or emphysema
- cough accompanied by excessive phlegm (mucus)

PREGNANCY OR BREAST FEEDING

If pregnant or breast-feeding, ask a health professional before use.

Keep out of reach of children.

Directions

adults and children 5 years and over - dissolve 1 lozenge slowly in mouth. Repeat every 2 hours as needed or as directed by a doctor.

children under 5 years - ask a doctor

Other information

- 6 calories per drop
- Excess consumption may cause a laxative effect.

INACTIVE INGREDIENT

Inactive ingredients: Acesulfame potasium (non-nutritive sweetener), artificial flavors, corn starch, eucalyptus oil, FD&C blue no. 1, FD&C red no. 40, glycerin, isomalt, maltitol syrup, medium chain triglycerides, soybean oil, sucralose (non-nutritive sweetener) and water.

QUESTIONS

Questions? Or to report an adverse event call 1-800-245-2898. Monday through Friday, 9am to 4pm EST